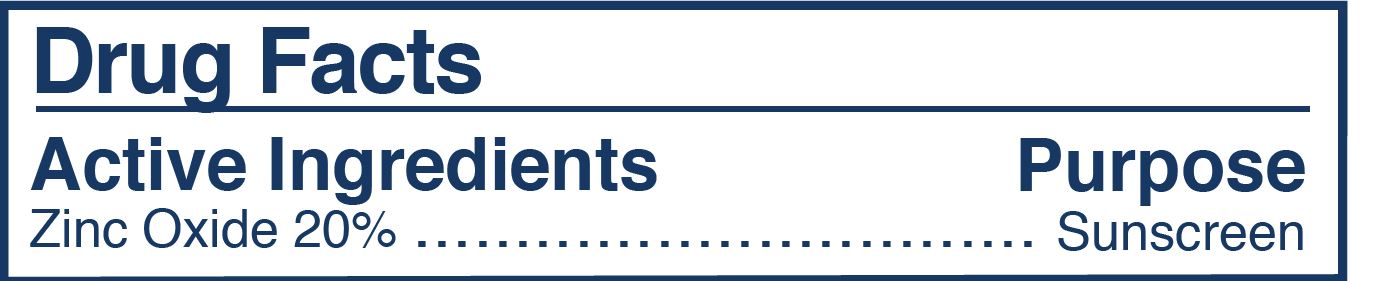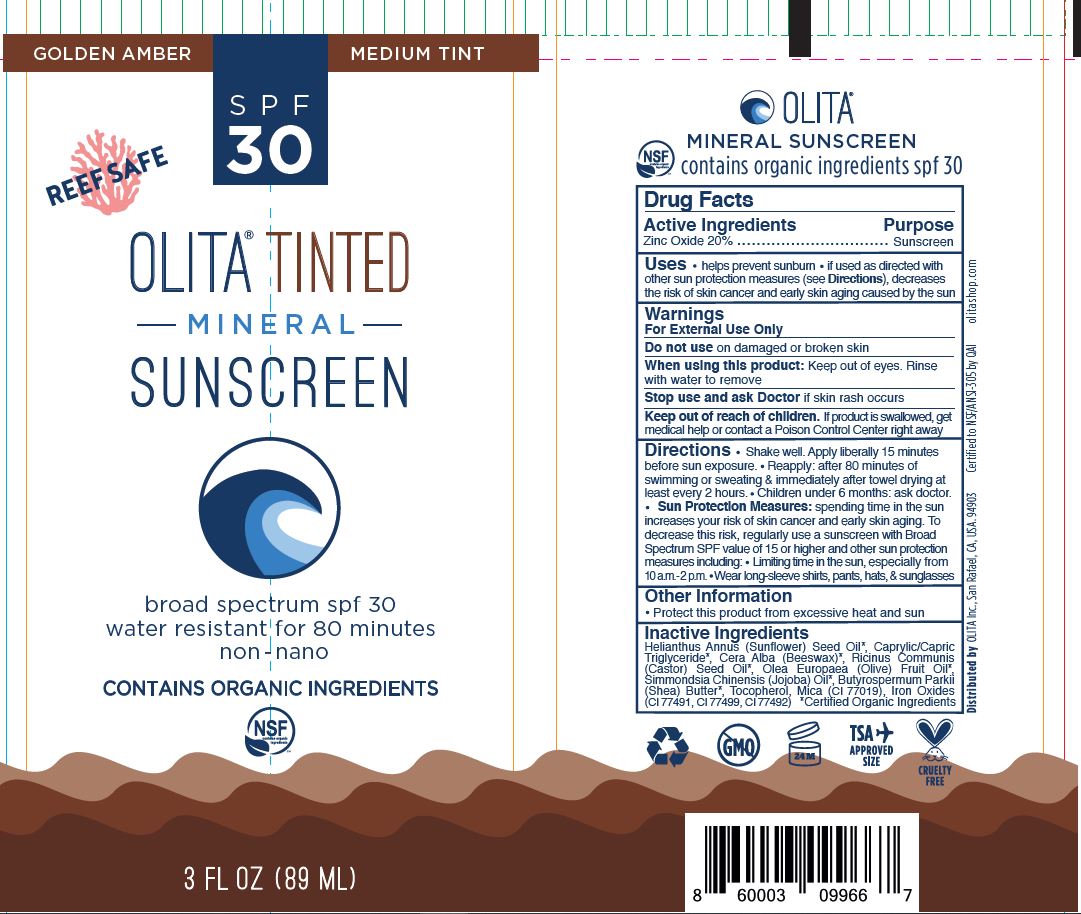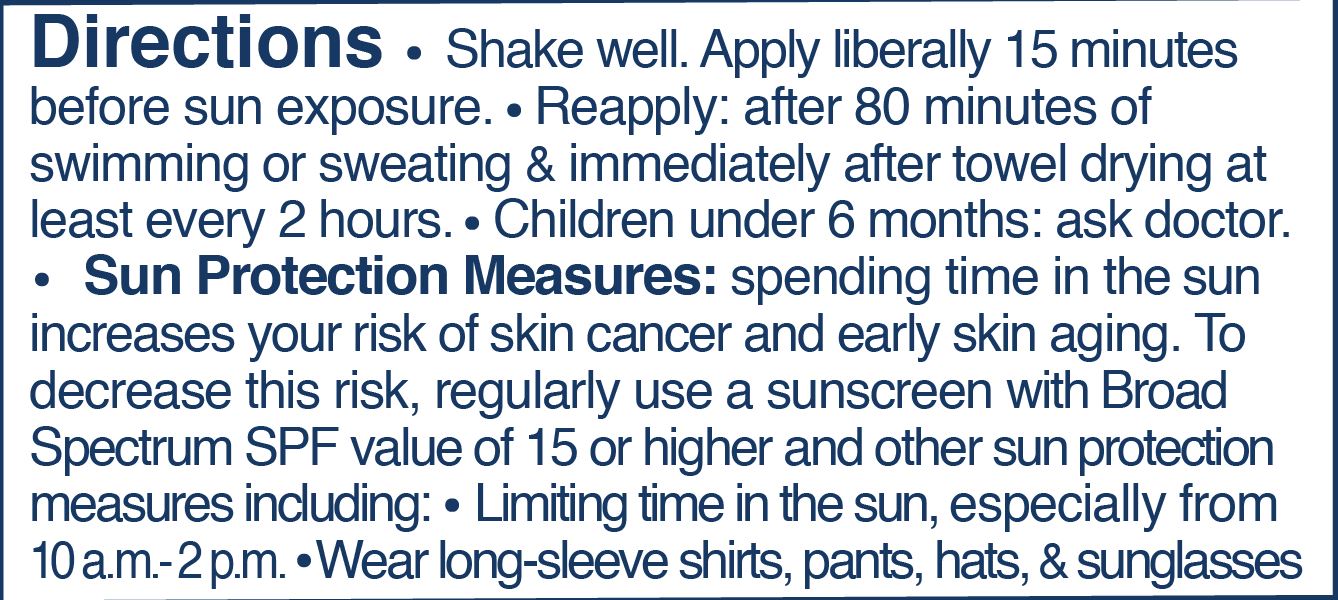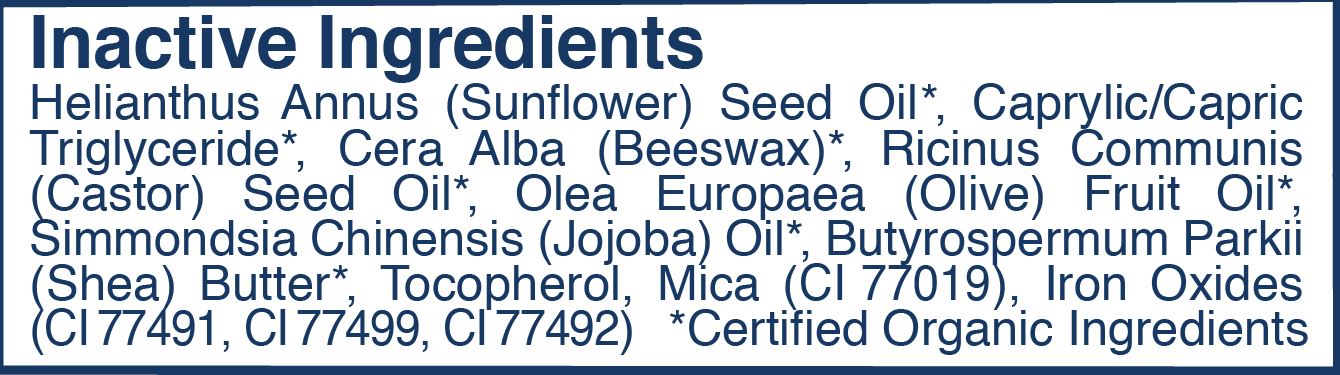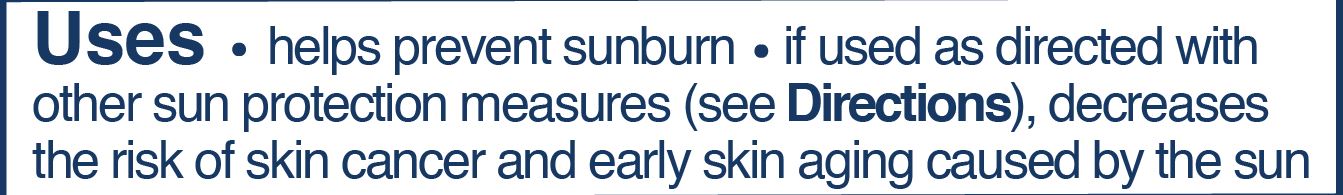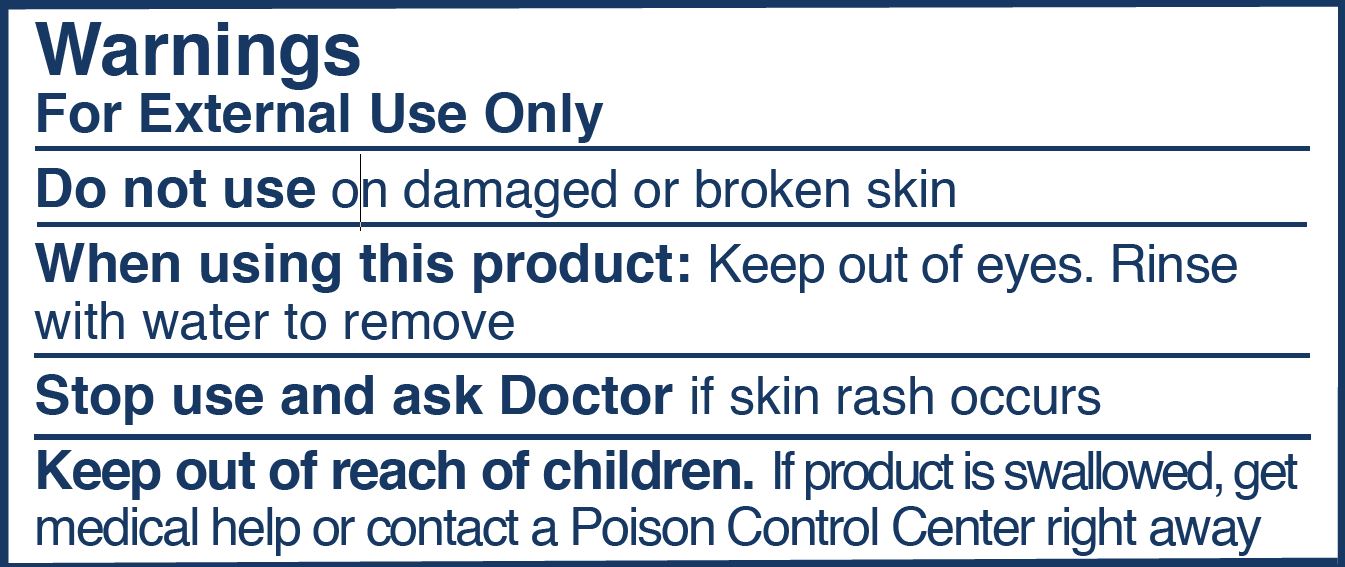 DRUG LABEL: Tinted Mineral Sunscreen, SPF 30 Medium Tint
NDC: 62932-262 | Form: OINTMENT
Manufacturer: Private Label Select Ltd CO
Category: otc | Type: HUMAN OTC DRUG LABEL
Date: 20211231

ACTIVE INGREDIENTS: ZINC OXIDE 20 g/100 g
INACTIVE INGREDIENTS: .DELTA.-TOCOPHEROL; WHITE WAX; OLIVE OIL; FERRIC OXYHYDROXIDE; JOJOBA OIL; SHEA BUTTER; MEDIUM-CHAIN TRIGLYCERIDES; .GAMMA.-TOCOPHEROL; FERRIC OXIDE RED; FERROSOFERRIC OXIDE; .BETA.-TOCOPHEROL; SUNFLOWER OIL; MICA; CASTOR OIL; .ALPHA.-TOCOPHEROL, D-

Olita Inc., Tinted Mineral Sunscreen, SPF 30 (Medium Tint)